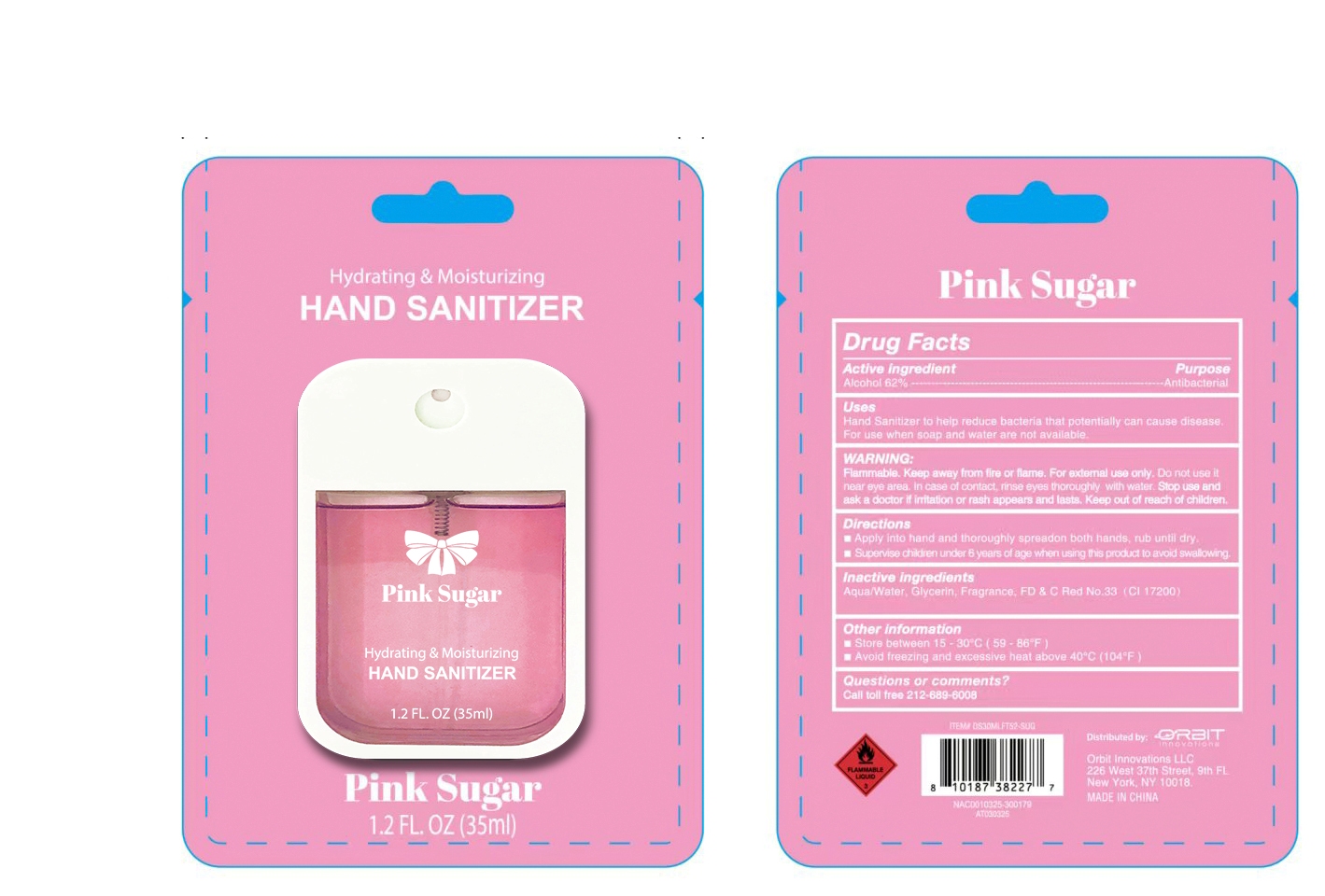 DRUG LABEL: Hydrating and Moisturizing Hand Sanitizer
NDC: 75112-010 | Form: SOLUTION
Manufacturer: Zhejiang Shenying Technology Co., Ltd. Jiaojiang Branch
Category: otc | Type: HUMAN OTC DRUG LABEL
Date: 20250416

ACTIVE INGREDIENTS: ALCOHOL 62 mL/100 mL
INACTIVE INGREDIENTS: GLYCERIN; WATER; D&C RED NO. 33

75112-010

Active Ingredient(s)

Alcohol 62%

Purpose

Antibacterial

Use

Hand sanitizer to help reduce bacteria that potentially can cause disease

For use when soap and water are not available

Warnings

For external use only

Flammable. Keep away from fire or flame. For external use only

Do not use near eye area. In case of cotact, rinse throughly with water

Stop use and ask a doctor if irritation or rash appears and lasts

Keep out of reach of children. If swallowed, get medical help or contact a Poison Control Center right away.

Directions

Apply into hand and thoroughly spread on both hands, rub untill dry

Supervise children under six years of age when using this product to avoid swallowing

Other information

Store between 15-30C (59-86F)

Avoid freezing and excessive heat about 40C (104F)

Inactive ingredients

Water, Glycerin, Fragrance, D&C Red No 33